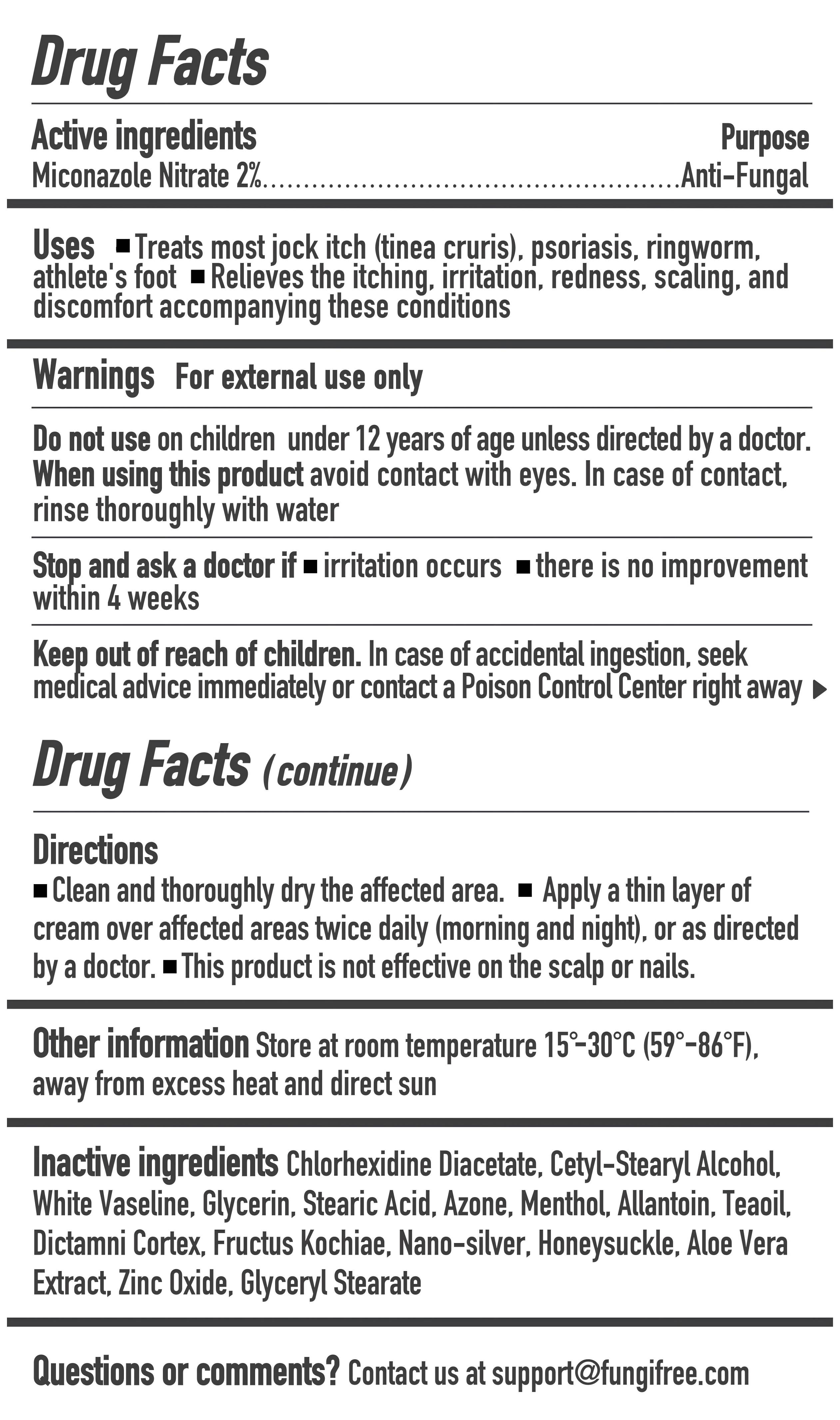 DRUG LABEL: FUNGIFREE Jock Itch Psoriasis Treatment Cream
NDC: 83364-021 | Form: CREAM
Manufacturer: YITONGBADA (SHENZHEN) INTERNATIONAL TRADE CO., LTD
Category: otc | Type: HUMAN OTC DRUG LABEL
Date: 20250924

ACTIVE INGREDIENTS: MICONAZOLE NITRATE 2 g/100 g
INACTIVE INGREDIENTS: DICTAMNUS DASYCARPUS ROOT; ALOE VERA LEAF; GLYCERYL STEARATE; CHLORHEXIDINE DIACETATE; STEARIC ACID; BASSIA SCOPARIA FRUIT; SILVER; ZINC OXIDE; WHITE PETROLATUM; CAMELLIA OIL; ALLANTOIN; CETOSTEARYL ALCOHOL; LAUROCAPRAM; GLYCERIN; MENTHOL; LONICERA CONFUSA FLOWER

FUNGIFREE Jock Itch & Psoriasis Treatment Cream

Drug Facts

Active ingredients

Miconazole Nitrate 2%

Purpose
Anti-Fungal

- Do not use it on children under 12 years of age unless directed by a doctor.

When using this product, avoid contact with eyes. In case of contact, rinse thoroughly with water.

ASK DOCTOR

Stop and ask a doctor if irritation occurs or there is no improvement within 4 weeks

Keep out of reach of children. In case of accidental ingestion, seek medical advice immediately or contact a Poison Control Center right away

USES
- Treats most jock itch (tinea cruris), psoriasis, ringworm, athlete's foot
- Relieves the itching, irritation, redness, scaling, and discomfort accompanying these conditions

WARNINGS
- For external use only

Directions
Clean and thoroughly dry the affected area.
Apply a thin layer of cream over affected areas twice daily (morning and night).or as directed by a doctor.
This product is not effective on the scalp or nails.

Other information
Store at room temperature 15°-30°C(59°-86°F), away from excess heat and direct sun

Inactive ingredients
Chlorhexidine Diacetate, Cetyl-Stearyl Alcohol, White Vaseline, Glycerin, Stearic Acid, Azone, Menthol, Allantoin, Teaoil, Dictamni Cortex, Fructus Kochiae, Nano-silver, Honeysuckle, Aloe Vera Extract, Zinc Oxide, Glyceryl Stearate